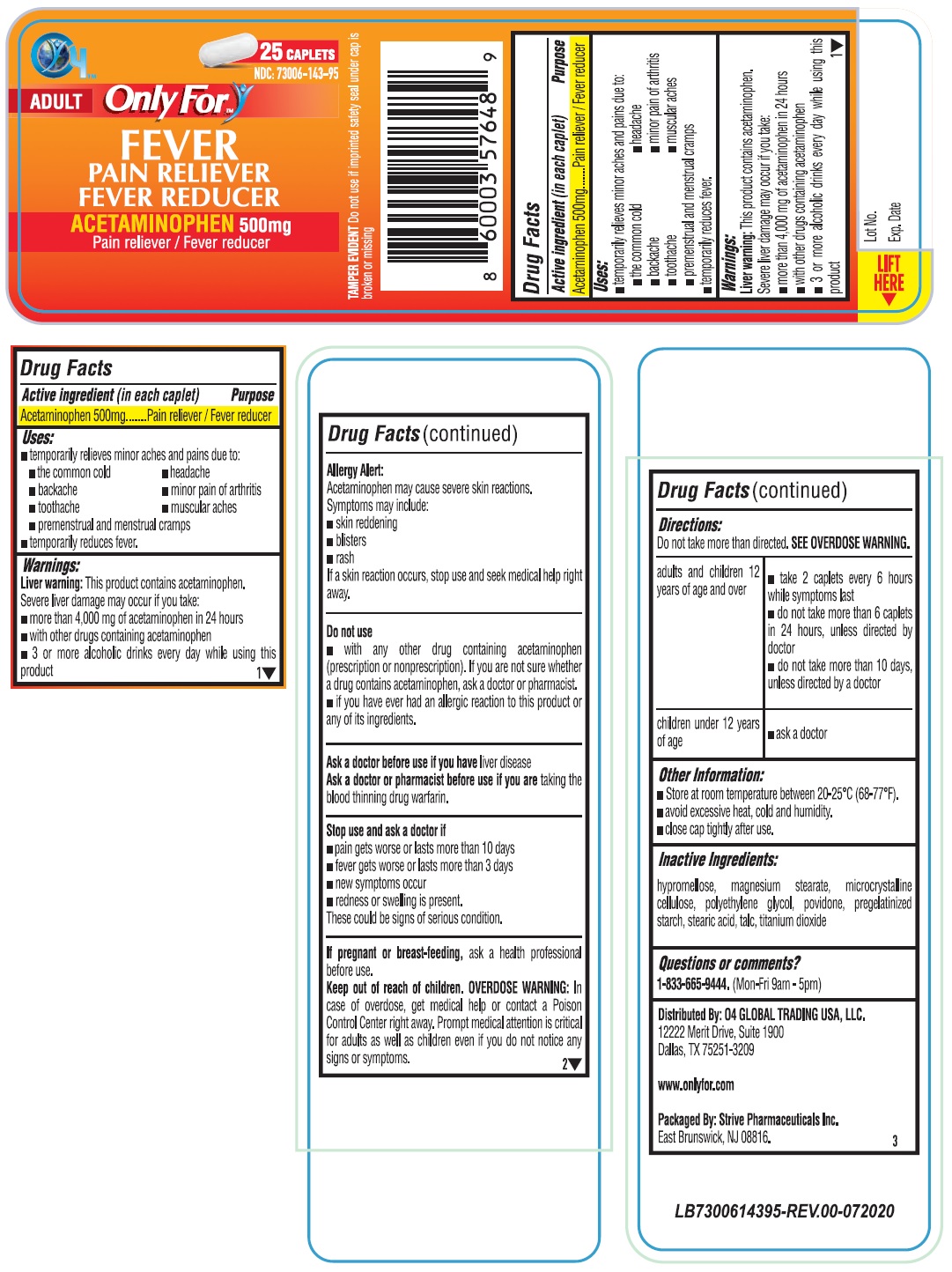 DRUG LABEL: Only For FEVER
NDC: 73006-143 | Form: TABLET
Manufacturer: O4 Global Trading Usa, Llc
Category: otc | Type: HUMAN OTC DRUG LABEL
Date: 20201119

ACTIVE INGREDIENTS: ACETAMINOPHEN 500 mg/1 1
INACTIVE INGREDIENTS: HYPROMELLOSE, UNSPECIFIED; MAGNESIUM STEARATE; MICROCRYSTALLINE CELLULOSE; POLYETHYLENE GLYCOL, UNSPECIFIED; POVIDONE, UNSPECIFIED; STARCH, CORN; STEARIC ACID; TALC; TITANIUM DIOXIDE

Only For™ FEVER

Active ingredient (in each caplet)

Acetaminophen 500mg

Purpose

Pain reliever / Fever reducer

Uses:

• temporarily relieves minor aches and pains due to:

• the common cold

• backache

• toothache

• premenstrual and menstrual cramps

• temporarily reduces fever.

• headache

• minor pain of arthritis

• muscular aches

• temporarily reduces fever.

Warnings:

Liver warning: This product contains acetaminophen. Severe liver damage may occur if you take:

• more than 4,000 mg of acetaminophen in 24 hours

• with other drugs containing acetaminophen

• 3 or more alcoholic drinks every day while using this product

Allergy Alert:

Acetaminophen may cause severe skin reactions.

Symptoms may include:

• skin reddening

• blisters

• rash

If a skin reaction occurs, stop use and seek medical help right away.

Do not use

• with any other drug containing acetaminophen (prescription or nonprescription). If you are not sure whether a drug contains acetaminophen, ask a doctor or pharmacist.

• if you have ever had any allergic reaction to this product or any of its ingredients.

Ask a doctor before use if you have liver disease

Ask a doctor or pharmacist before use if are taking the blood thinning drug warfarin

Stop use and ask a doctor if

• pain gets worse or lasts more than 10 days

• fever gets worse or last more than 3 days

• new symptoms occur.

• redness or swelling is present

These could be signs of a serious condition.

If pregnant or breast-feeding, ask a health professional before use.

Keep out of reach of children. OVERDOSE WARNING: In case of overdose, get medical help or contact a Poison Control Center right away. Prompt medical attention is critical for adults as well as for children even if you do not notice any signs or symptoms.

Directions:

Do not take more than directed. SEE OVERDOSE WARNING.

adults and children 12 years of age and over | • take 2 caplets every 6 hours while symptoms last; • do not take more than 6 caplets in 24 hours, unless directed by doctor; • do not take more than 10 days, unless directed by a doctor
children under 12 years of age | • ask a doctor

Other Information:

• Store at room temperature between 20-25°C (68-77°F).

• avoid excessive heat, cold and humidity.

• close cap tightly after use.

Inactive Ingredients:

hypromellose, magnesium stearate, microcrystalline cellulose, polyethylene glycol, povidone, pregelatinized starch, stearic acid, talc, titanium dioxide

Questions or comments?

1-833-665-9444. (Mon-Fri 9am-5pm)

ADULT

PAIN RELIEVER FEVER REDUCER

TAMPER EVIDENT: Do not use if imprinted safety seal under cap is broken or missing

Distributed By: O4 GLOBAL TRADING USA, LLC.

12222 Merit Drive, Suite 1900

Dallas, TX 75251-3209

www.onlyfor.com

Packaged By: Strive Pharmaceuticals Inc.

East Brunswick, NJ 08816.